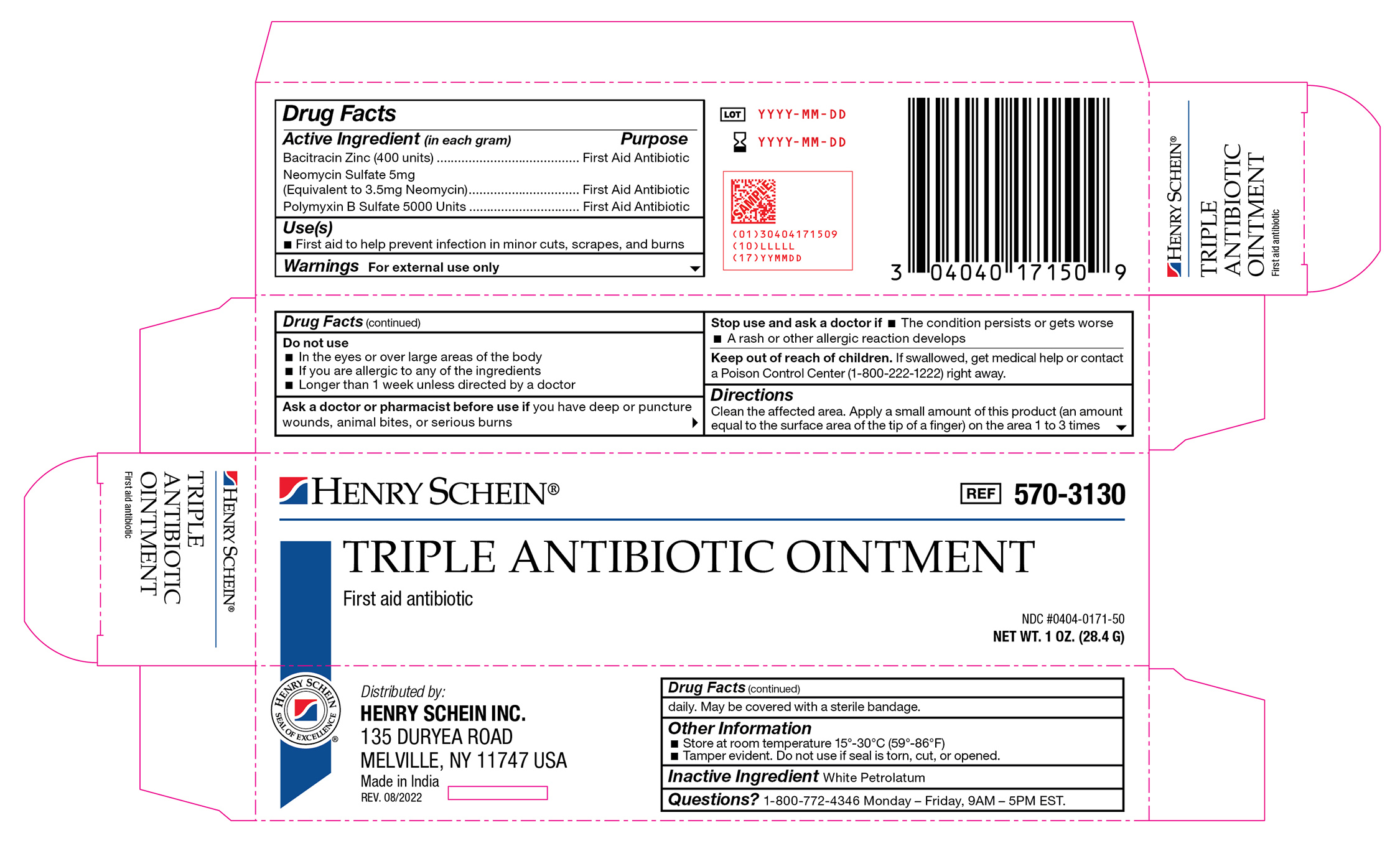 DRUG LABEL: Bacitracin Zinc, Polymyxin B Sulfate, and Neomycin Sulfate
NDC: 0404-0171 | Form: OINTMENT
Manufacturer: Henry Schein
Category: otc | Type: HUMAN OTC DRUG LABEL
Date: 20251125

ACTIVE INGREDIENTS: POLYMYXIN B SULFATE 50000 [iU]/1 g; NEOMYCIN SULFATE 5 mg/1 g; BACITRACIN ZINC 400 [iU]/1 g
INACTIVE INGREDIENTS: WHITE PETROLATUM

570-3130 Triple Antibiotic NDC 0404-0171-50

Active Ingredient

Bacitracin Zinc (400 units)

Neomycin Sulfate 5mg (Equivalent to 3.5mg Neomycin)

Polymyxin B Sulfate 5000 Units

Purpose

First Aid Antibiotic

Use(s)

First aid to prevent infection in minor cuts, scrapes, and burns

Warnings

For External Use Only

Do not use

• In the eyes or over large areas of the body

• If you are allergic to any of the ingredients

• Longer than 1 week unless directed by a doctor

Ask a doctor before use if you have

Deep or puncture wounds, animal bites, or serious burns.

Stop use and ask a doctor if

• The condition persists or gets worse

• A rash or other allergic reaction develops

Keep our of reach of children

If swallowed, get medical help or contract a Poison Control Center (1-800-222-1222) right away.

Directions

Clean the affected area. Apply a small amount of this product (an amount equal to the surface area of the tip of a finger) on the area 1 to 3 times daily. May be covered with a sterile bandage.

Other Information

• Store at room temperature 15º-30ºC (59º-86ºF)

• Tamper evident. Do not use if seal if torn, cut, or opened.

Inactive Ingredients

White Petrolatum